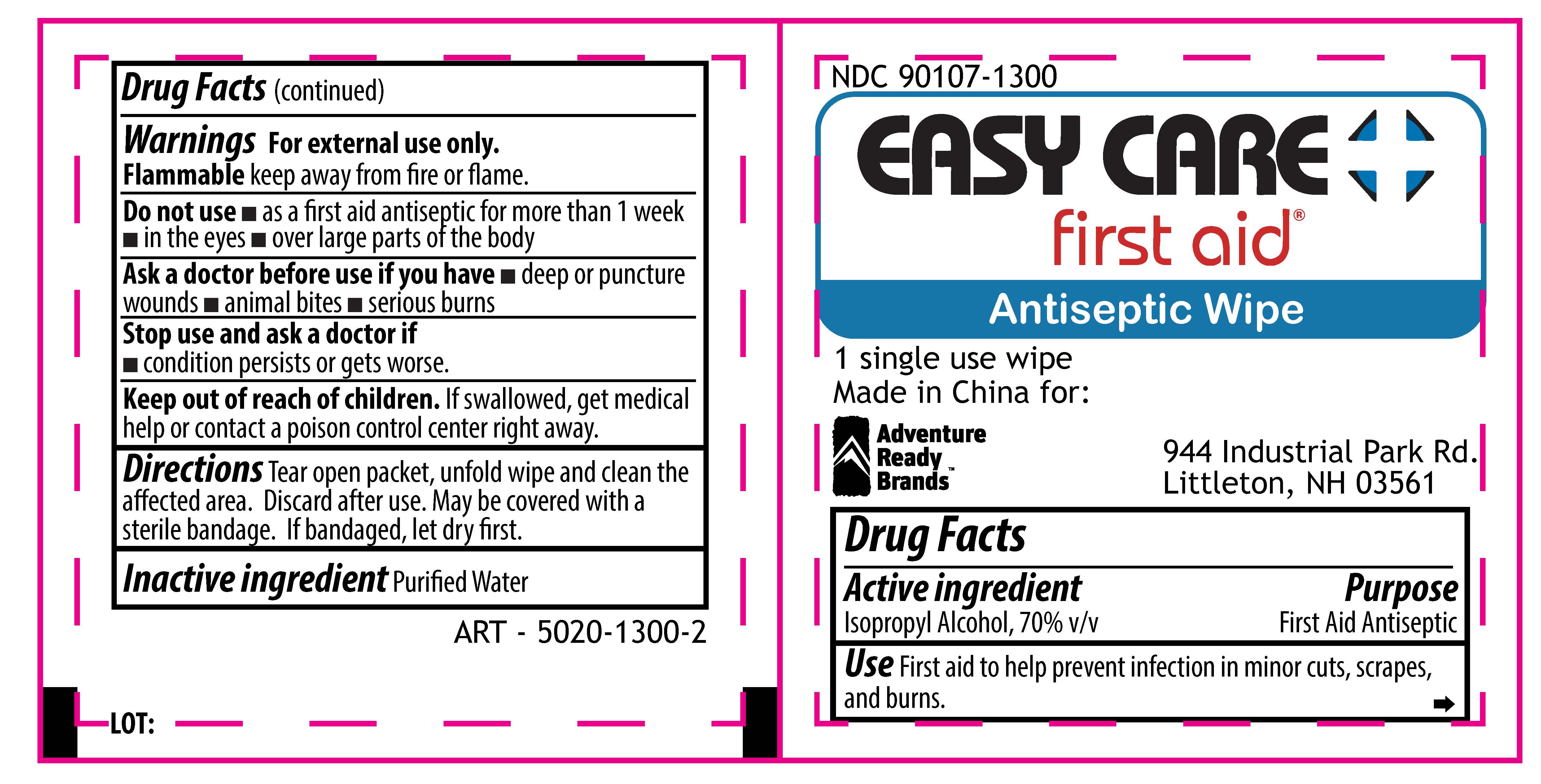 DRUG LABEL: Easy Care First Aid Antiseptic Wipe
NDC: 90107-1300 | Form: SWAB
Manufacturer: Adventure Ready Brands
Category: otc | Type: HUMAN OTC DRUG LABEL
Date: 20201210

ACTIVE INGREDIENTS: ISOPROPYL ALCOHOL 70 mL/100 mL
INACTIVE INGREDIENTS: WATER

Easy Care Antiseptic Wipe

Active Ingredient

Isopropyl Alcohol, 70% v/v

Purpose

First Aid Antiseptic

Use

First aid to help prevent infection in minor cuts, scrapes, and burns.

Warnings

For external use only.

Flammable - keep away from fire or flame

Do not use

- As a first aid antiseptic for more than 1 week
- in the eyes
- over large parts of the body

Ask a doctor before use if you have

- deep or puncture wounds
- animal bites
- over large parts of the body

Stop use and ask a doctor if

- irritation and redness develop and persist for more than 72 hours

Keep out of reach of children.

If swallowed, get medical help or contact a Poison Control Center right away.

Other information

Store at room temperature 15-30 degree Celsius (59-86 degree Fahrenheit)

Directions

Tear open packet, unfold wipe, and clean the affected area. Discard after use. May be covered with a sterile bandage. If bandaged, let dry first.

Inactive Ingredient

Purified water.

PACKAGE LABEL

Easy Care First Aid® Antiseptic Wipe

Made in China for:

Adventure Ready Brands

944 Industrial Park Rd.

Littleton, NH 03561

1 single use wipe